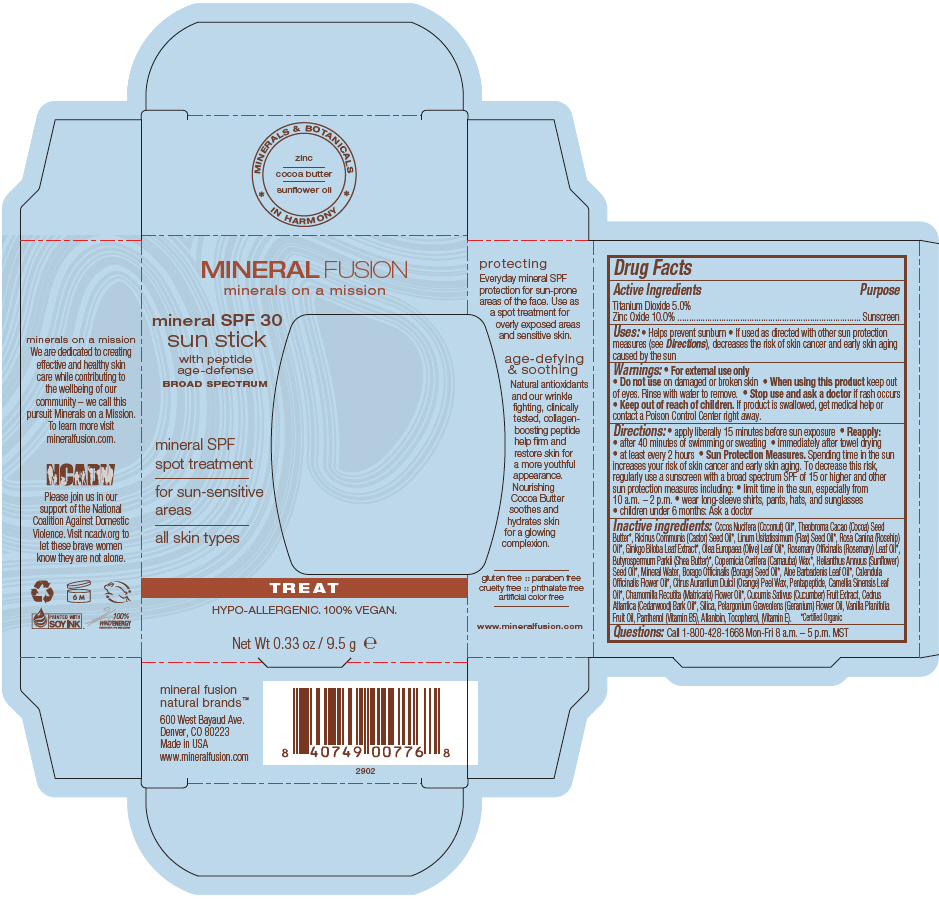 DRUG LABEL: MINERAL SPF 30 SUN
NDC: 55789-2902 | Form: STICK
Manufacturer: Mineral Fusion Natural Brands
Category: otc | Type: HUMAN OTC DRUG LABEL
Date: 20150821

ACTIVE INGREDIENTS: TITANIUM DIOXIDE 0.475 g/9.5 g; ZINC OXIDE 0.95 g/9.5 g
INACTIVE INGREDIENTS: COCONUT OIL 5.7 g/9.5 g; COCOA BUTTER; CASTOR OIL; LINSEED OIL; ROSA CANINA FLOWER OIL; GINKGO; OLIVE OIL; ROSEMARY; SHEANUT OIL; CARNAUBA WAX; SUNFLOWER OIL; WATER; BORAGE OIL; ALOE VERA LEAF; CALENDULA OFFICINALIS FLOWER; CITRUS SINENSIS FLOWER WAX; THYMOPENTIN; TEA LEAF OIL; CHAMOMILE FLOWER OIL; CUCUMIS SATIVUS LEAF; CEDRUS ATLANTICA BARK OIL; SILICON DIOXIDE; PELARGONIUM GRAVEOLENS FLOWER OIL; VANILLA PLANIFOLIA OIL; PANTHENOL; ALLANTOIN; TOCOPHEROL

MINERAL SPF 30 SUN STICK

Drug Facts

Active Ingredients

Titanium Dioxide 5.0%
Zinc Oxide 10.0%

Purpose

Sunscreen

Uses

- Helps prevent sunburn
- If used as directed with other sun protection measures (see Directions), decreases the risk of skin cancer and early skin aging caused by the sun

Warnings

- For external use only

- Do not use on damaged or broken skin

- When using this product keep out of eyes. Rinse with water to remove.

- Stop use and ask a doctor if rash occurs

- Keep out of reach of children. If product is swallowed, get medical help or contact a Poison Control Center right away.

Directions

- apply liberally 15 minutes before sun exposure
- Reapply:
  - after 40 minutes of swimming or sweating
  - immediately after towel drying
  - at least every 2 hours
- Sun Protection Measures. Spending time in the sun increases your risk of skin cancer and early skin aging. To decrease this risk, regularly use a sunscreen with a broad spectrum SPF of 15 or higher and other sun protection measures including:
  - limit time in the sun, especially from 10 a.m. – 2 p.m.
  - wear long-sleeve shirts, pants, hats, and sunglasses
- children under 6 months: Ask a doctor

Inactive ingredients

Cocos Nucifera (Coconut) Oil [Certified Organic] , Theobroma Cacao (Cocoa) Seed Butter, Ricinus Communis (Castor) Seed Oil*, Linum Usitatissimum (Flax) Seed Oil, Rosa Canina (Rosehip) Oil, Ginkgo Biloba Leaf Extract, Olea Europaea (Olive) Leaf Oil, Rosemary Officinalis (Rosemary) Leaf Oil, Butyrospermum Parkii (Shea Butter), Copernicia Cerifera (Carnauba) Wax, Helianthus Annuus (Sunflower) Seed Oil, Mineral Water, Borago Officinalis (Borage) Seed Oil, Aloe Barbadenis Leaf Oil, Calendula Officinalis Flower Oil, Citrus Aurantium Dulcil (Orange) Peel Wax, Pentapeptide, Camellia Sinensis Leaf Oil, Chamomilla Recutita (Matricaria) Flower Oil, Cucumis Sativus (Cucumber) Fruit Extract, Cedrus Atlantica (Cedarwood) Bark Oil, Silica, Pelargonium Graveolens (Geranium) Flower Oil, Vanilla Planifolia Fruit Oil, Panthenol (Vitamin B5), Allantoin, Tocopherol, (Vitamin E).

Questions

Call 1-800-428-1668 Mon-Fri 8 a.m. – 5 p.m. MST

PRINCIPAL DISPLAY PANEL - 9.5 g Cylinder Carton

MINERAL FUSION
minerals on a mission

mineral SPF 30
sun stick
with peptide
age-defense
BROAD SPECTRUM

mineral SPF
spot treatment

for sun-sensitive
areas

all skin types

TREAT

HYPO-ALLERGENIC. 100% VEGAN.

Net Wt 0.33 oz / 9.5 g e